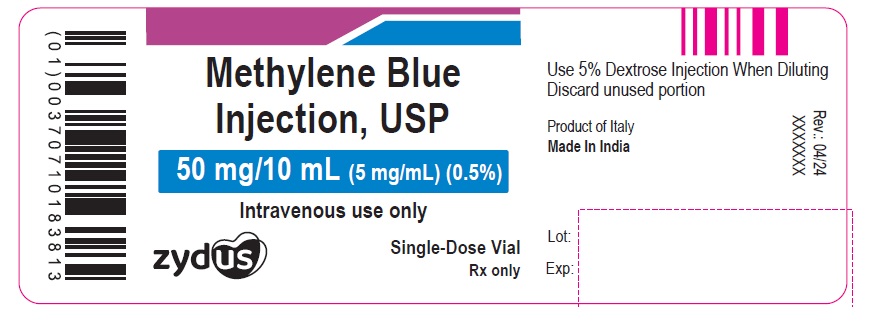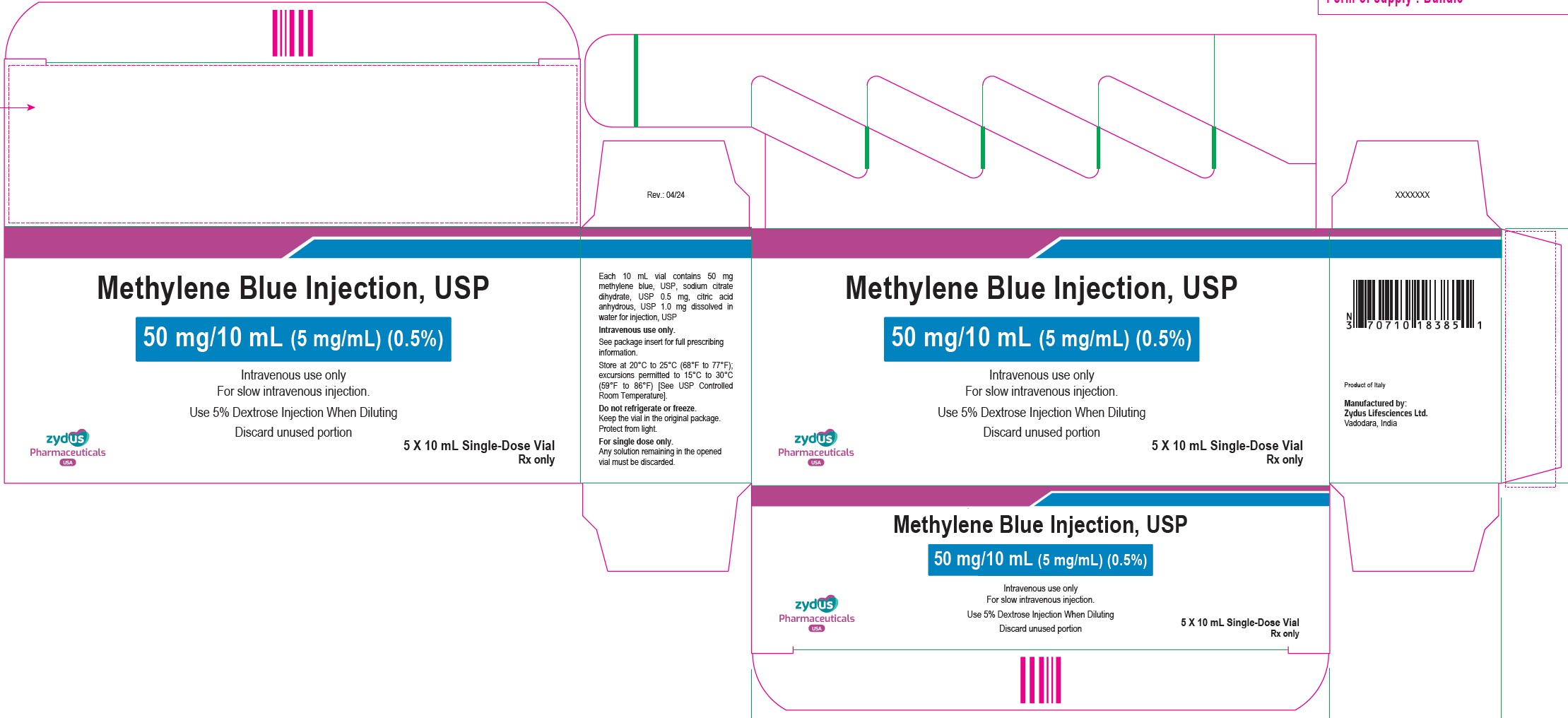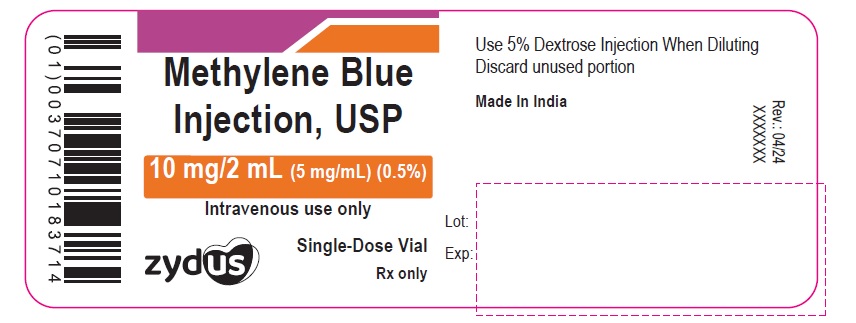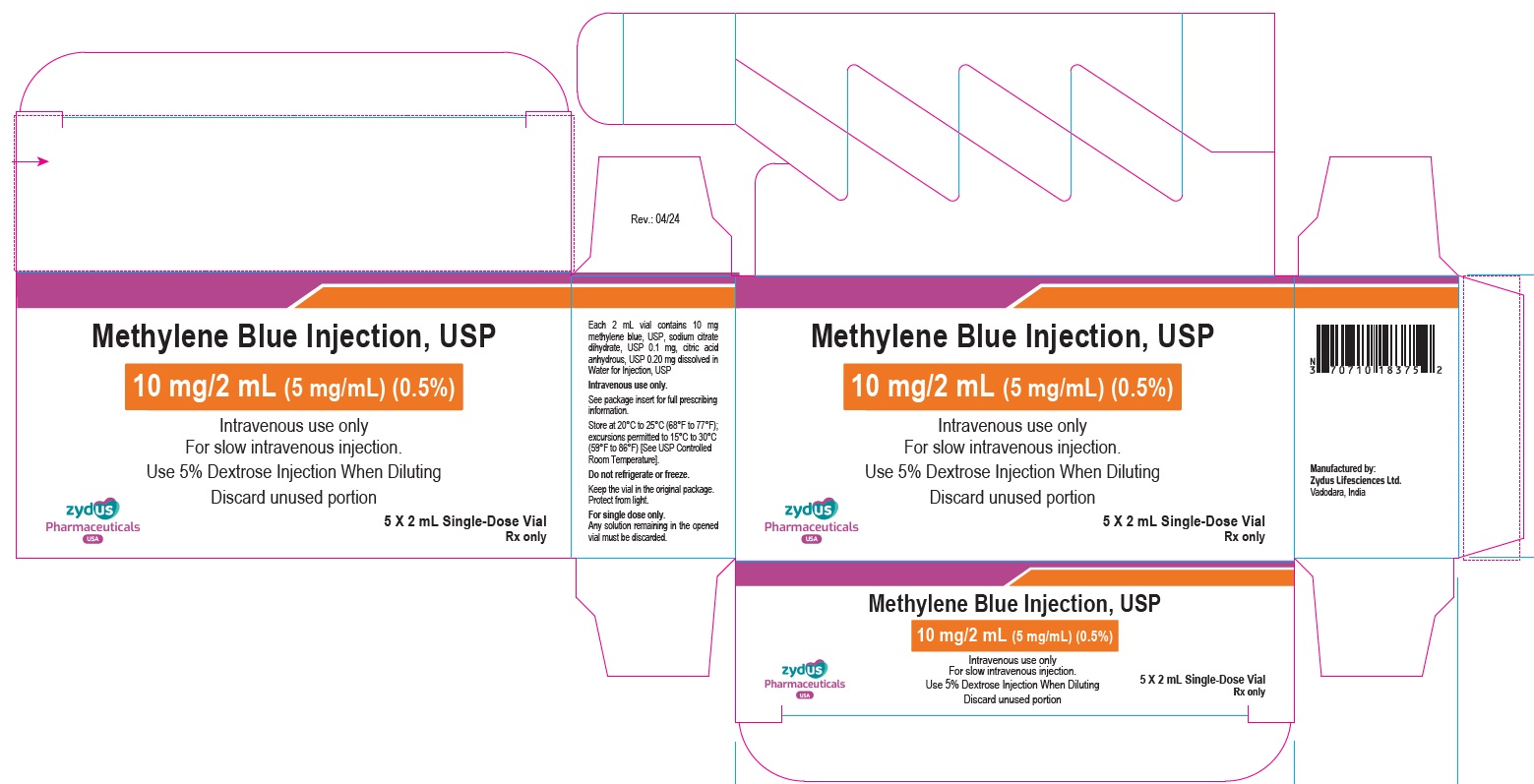 DRUG LABEL: Methylene blue
NDC: 70771-1767 | Form: INJECTION
Manufacturer: Zydus Lifesciences Limited
Category: prescription | Type: HUMAN PRESCRIPTION DRUG LABEL
Date: 20240424

ACTIVE INGREDIENTS: METHYLENE BLUE 5 mg/1 mL
INACTIVE INGREDIENTS: TRISODIUM CITRATE DIHYDRATE; ANHYDROUS CITRIC ACID; WATER

Methylene Blue Injection, USP

PACKAGE LABEL.PRINCIPAL DISPLAY PANEL

NDC 70771-1768-1

Methylene Blue Injection, USP

50 mg/10 mL (5 mg/mL)

Intravenous use only

Single-Dose vial

Rx only

NDC 70771-1768-5

Methylene Blue Injection, USP

50 mg/10 mL (5 mg/mL)

Intravenous use only

5 X 10 mL Single-Dose Vial

Rx only

NDC 70771-1767-1

Methylene Blue Injection, USP

10 mg/2 mL (5 mg/mL)

Intravenous use only

Single-Dose vial

Rx only

NDC 70771-1767-5

Methylene Blue Injection, USP

10 mg/2 mL (5 mg/mL)

Intravenous use only

5 X 2 mL Single-Dose Vial

Rx only